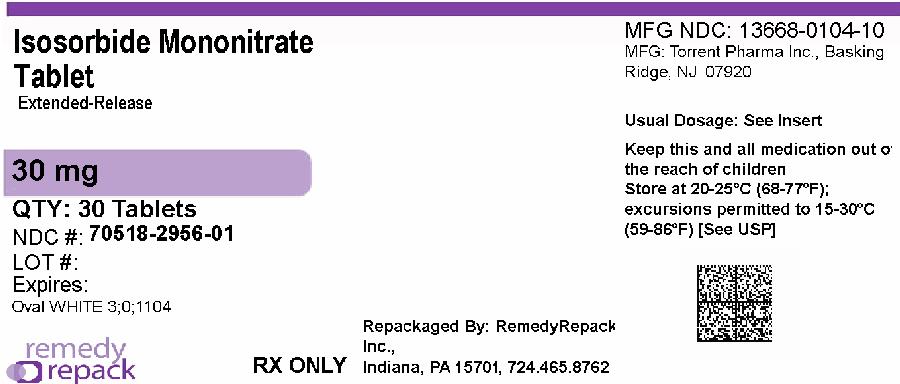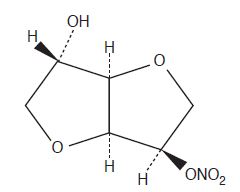 DRUG LABEL: ISOSORBIDE MONONITRATE
NDC: 70518-2956 | Form: TABLET, EXTENDED RELEASE
Manufacturer: REMEDYREPACK INC.
Category: prescription | Type: HUMAN PRESCRIPTION DRUG LABEL
Date: 20260213

ACTIVE INGREDIENTS: ISOSORBIDE MONONITRATE 30 mg/1 1
INACTIVE INGREDIENTS: DIETHYL PHTHALATE; CELLULOSE, MICROCRYSTALLINE; HYDROGENATED CASTOR OIL; HYDROXYPROPYL CELLULOSE (1600000 WAMW); HYPROMELLOSE 2910 (6 MPA.S); LACTOSE MONOHYDRATE; MAGNESIUM STEARATE; SILICON DIOXIDE; TALC; TITANIUM DIOXIDE

Isosorbide Mononitrate Extended-Release Tablets, USP
Rx only

DESCRIPTION

Isosorbide mononitrate (ISMN), an organic nitrate and the major biologically active metabolite of isosorbide dinitrate (ISDN), is a vasodilator with effects on both arteries and veins.

Each tablet, for oral administration, contains either 30 mg, 60 mg or 120 mg of isosorbide mononitrate in an extended-release formulation. In addition, each tablet contains the following inactive ingredients: colloidal silicon dioxide, diethyl phthalate, hydrogenated castor oil, hydroxypropyl cellulose, hypromellose, lactose monohydrate, magnesium stearate, microcrystalline cellulose, talc and titanium dioxide.

The molecular formula of ISMN is C6H9NO6and the molecular weight is 191.14. The chemical name for ISMN is 1,4:3,6-dianhydro-,D-glucitol 5-nitrate; the compound has the following structural formula:

ISMN is a white, crystalline, odorless compound which is stable in air and in solution, has a melting point of about 90°C, and an optical rotation of +144° (2% in water, 20°C).

Isosorbide mononitrate is freely soluble in water, ethanol, methanol, chloroform, ethyl acetate, and dichloromethane.

For 30 mg: Meets USP Dissolution Test 6.

For 60 mg and 120 mg: Meets USP Dissolution Test 1.

CLINICAL PHARMACOLOGY

Mechanism of Action

The isosorbide mononitrate extended-release tablet is an oral extended-release formulation of ISMN, the major active metabolite of isosorbide dinitrate; most of the clinical activity of the dinitrate is attributable to the mononitrate.

The principal pharmacological action of ISMN and all organic nitrates in general is relaxation of vascular smooth muscle, producing dilatation of peripheral arteries and veins, especially the latter. Dilatation of the veins promotes peripheral pooling of blood, decreases venous return to the heart, thereby reducing left ventricular end-diastolic pressure and pulmonary capillary wedge pressure (preload). Arteriolar relaxation reduces systemic vascular resistance, systolic arterial pressure and mean arterial pressure (afterload). Dilatation of the coronary arteries also occurs. The relative importance of preload reduction, afterload reduction, and coronary dilatation remains undefined.

Pharmacodynamics

Dosing regimens for most chronically used drugs are designed to provide plasma concentrations that are continuously greater than a minimally effective concentration. This strategy is inappropriate for organic nitrates. Several well-controlled clinical trials have used exercise testing to assess the antianginal efficacy of continuously delivered nitrates. In the large majority of these trials, active agents were indistinguishable from placebo after 24 hours (or less) of continuous therapy. Attempts to overcome tolerance by dose escalation, even to doses far in excess of those used acutely, have consistently failed. Only after nitrates have been absent from the body for several hours has their antianginal efficacy been restored. Isosorbide mononitrate extended-release tablets, during long-term use over 42 days dosed at 120 mg once daily, continued to improve exercise performance at 4 hours and at 12 hours after dosing but its effects (although better than placebo) are less than or at best equal to the effects of the first dose of 60 mg.

Pharmacokinetics and Metabolism

After oral administration of ISMN as a solution or immediate-release tablets, maximum plasma concentrations of ISMN are achieved in 30 to 60 minutes, with an absolute bioavailability of approximately 100%. After intravenous administration, ISMN is distributed into total body water in about 9 minutes with a volume of distribution of approximately 0.6-0.7 L/kg. Isosorbide mononitrate is approximately 5% bound to human plasma proteins and is distributed into blood cells and saliva. Isosorbide mononitrate is primarily metabolized by the liver, but unlike oral isosorbide dinitrate, it is not subject to first-pass metabolism. Isosorbide mononitrate is cleared by denitration to isosorbide and glucuronidation as the mononitrate, with 96% of the administered dose excreted in the urine within 5 days and only about 1% eliminated in the feces. At least six different compounds have been detected in urine, with about 2% of the dose excreted as the unchanged drug and at least five metabolites. The metabolites are not pharmacologically active. Renal clearance accounts for only about 4% of total body clearance. The mean plasma elimination half-life of ISMN is approximately 5 hours.

The disposition of ISMN in patients with various degrees of renal insufficiency, liver cirrhosis, or cardiac dysfunction was evaluated and found to be similar to that observed in healthy subjects. The elimination half-life of ISMN was not prolonged, and there was no drug accumulation in patients with chronic renal failure after multiple oral dosing.

The pharmacokinetics and/or bioavailability of isosorbide mononitrate extended-release tablets have been studied in both normal volunteers and patients following single- and multiple-dose administration. Data from these studies suggest that the pharmacokinetics of ISMN administered as isosorbide mononitrate extended-release tablets are similar between normal healthy volunteers and patients with angina pectoris. In single- and multiple-dose studies, the pharmacokinetics of ISMN were dose proportional between 30 mg and 240 mg.

In a multiple-dose study, the effect of age on the pharmacokinetic profile of isosorbide mononitrate extended-release tablets 60 mg and 120 mg (2 x 60 mg) was evaluated in subjects ≥45 years. The results of that study indicate that there are no significant differences in any of the pharmacokinetic variables of ISMN between elderly (≥65 years) and younger individuals (45–64 years) for the isosorbide mononitrate extended-release 60 mg dose. The administration of isosorbide mononitrate extended-release 120 mg (2 x 60 mg tablets every 24 hours for 7 days) produced a dose-proportional increase in Cmaxand AUC, without changes in Tmaxor the terminal half-life. The older group (65-74 years) showed 30% lower apparent oral clearance (Cl/F) following the higher dose, i.e., 120 mg, compared to the younger group (45-64 years); Cl/F was not different between the two groups following the 60 mg regimen. While Cl/F was independent of dose in the younger group, the older group showed slightly lower Cl/F following the 120 mg regimen compared to the 60 mg regimen. Differences between the two age groups, however, were not statistically significant. In the same study, females showed a slight (15%) reduction in clearance when the dose was increased. Females showed higher AUCs and Cmaxcompared to males, but these differences were accounted for by differences in body weight between the two groups. When the data were analyzed using age as a variable, the results indicated that there were no significant differences in any of the pharmacokinetic variables of ISMN between older (≥65 years) and younger individuals (45-64 years). The results of this study, however, should be viewed with caution due to the small number of subjects in each age subgroup and consequently the lack of sufficient statistical power.

The following table summarizes key pharmacokinetic parameters of ISMN after single- and multiple-dose administration of ISMN as an oral solution or isosorbide mononitrate extended-release tablets:

 | SINGLE-DOSE STUDIES |  | MULTIPLE-DOSE STUDIES
PARAMETER | ISMN 60 mg | ISMN Extended-Release Tablets 60 mg | ISMN Extended-Release Tablets 60 mg | ISMN Extended-Release Tablets 120 mg
Cmax(ng/mL) | 1242-1534 | 424-541 | 557-572 | 1151-1180
Tmax(hr) | 0.6-0.7 | 3.1-4.5 | 2.9-4.2 | 3.1-3.2
AUC (ng•hr/mL) | 8189-8313 | 5990-7452 | 6625-7555 | 14241-16800
T½ (hr) | 4.8-5.1 | 6.3-6.6 | 6.2-6.3 | 6.2-6.4
Cl/F (mL/min) | 120-122 | 151-187 | 132-151 | 119-140

Food Effects

The influence of food on the bioavailability of ISMN after single-dose administration of isosorbide mononitrate extended-release tablets 60 mg was evaluated in three different studies involving either a "light" breakfast or a high-calorie, high-fat breakfast. Results of these studies indicate that concomitant food intake may decrease the rate (increase in Tmax) but not the extent (AUC) of absorption of ISMN.

Clinical Trials

Controlled trials with isosorbide mononitrate extended-release tablets have demonstrated antianginal activity following acute and chronic dosing. Administration of isosorbide mononitrate extended-release tablets once daily, taken early in the morning on arising, provided at least 12 hours of antianginal activity.

In a placebo-controlled parallel study, 30, 60, 120 and 240 mg of isosorbide mononitrate extended-release tablets were administered once daily for up to 6 weeks. Prior to randomization, all patients completed a 1- to 3-week single-blind placebo phase to demonstrate nitrate responsiveness and total exercise treadmill time reproducibility. Exercise tolerance tests using the Bruce Protocol were conducted prior to and at 4 and 12 hours after the morning dose on days 1, 7, 14, 28 and 42 of the double-blind period. Isosorbide mononitrate extended-release tablets 30 and 60 mg (only doses evaluated acutely) demonstrated a significant increase from baseline in total treadmill time relative to placebo at 4 and 12 hours after the administration of the first dose. At day 42, the 120 and 240 mg dose of isosorbide mononitrate extended-release tablets demonstrated a significant increase in total treadmill time at 4 and 12 hours post dosing, but by day 42, the 30 and 60 mg doses no longer were differentiable from placebo. Throughout chronic dosing, rebound was not observed in any isosorbide mononitrate extended-release treatment group.

Pooled data from two other trials, comparing isosorbide mononitrate extended-release tablets 60 mg once daily, ISDN 30 mg QID, and placebo QID in patients with chronic stable angina using a randomized, double-blind, three-way crossover design found statistically significant increases in exercise tolerance times for isosorbide mononitrate extended-release tablets compared to placebo at hours 4, 8 and 12 and to ISDN at hour 4. The increases in exercise tolerance on day 14, although statistically significant compared to placebo, were about half of that seen on day 1 of the trial.

INDICATIONS AND USAGE

Isosorbide mononitrate extended-release tablets, USP are indicated for the prevention of angina pectoris due to coronary artery disease. The onset of action of oral isosorbide mononitrate is not sufficiently rapid for this product to be useful in aborting an acute anginal episode.

CONTRAINDICATIONS

Isosorbide mononitrate extended-release tablets are contraindicated in patients who have shown hypersensitivity or idiosyncratic reactions to other nitrates or nitrites.

PRECAUTIONS

Information for Patients

Patients should be told that the antianginal efficacy of isosorbide mononitrate extended-release tablets can be maintained by carefully following the prescribed schedule of dosing. For most patients, this can be accomplished by taking the dose on arising.

As with other nitrates, daily headaches sometimes accompany treatment with isosorbide mononitrate. In patients who get these headaches, the headaches are a marker of the activity of the drug. Patients should resist the temptation to avoid headaches by altering the schedule of their treatment with isosorbide mononitrate, since loss of headache may be associated with simultaneous loss of antianginal efficacy. Aspirin or acetaminophen often successfully relieves isosorbide mononitrate-induced headaches with no deleterious effect on isosorbide mononitrate’s antianginal efficacy.

Treatment with isosorbide mononitrate may be associated with lightheadedness on standing, especially just after rising from a recumbent or seated position. This effect may be more frequent in patients who have also consumed alcohol.

Drug Interactions

The vasodilating effects of isosorbide mononitrate may be additive with those of other vasodilators. Alcohol, in particular, has been found to exhibit additive effects of this variety. Marked symptomatic orthostatic hypotension has been reported when calcium channel blockers and organic nitrates were used in combination. Dose adjustments of either class of agents may be necessary.

Drug/Laboratory Test Interactions

Nitrates and nitrites may interfere with the Zlatkis-Zak color reaction, causing falsely low readings in serum cholesterol determinations.

Carcinogenesis, Mutagenesis, Impairment of Fertility

No evidence of carcinogenicity was observed in rats exposed to isosorbide mononitrate in their diets at doses of up to 900 mg/kg/day for the first 6 months and 500 mg/kg/day for the remaining duration of a study in which males were dosed for up to 121 weeks and females were dosed for up to 137 weeks. No evidence of carcinogenicity was observed in mice exposed to isosorbide mononitrate in their diets for up to 104 weeks at doses of up to 900 mg/kg/day.

Isosorbide mononitrate did not produce gene mutations (Ames test, mouse lymphoma test) or chromosome aberrations (human lymphocyte and mouse micronucleus tests) at biologically relevant concentrations.

No effects on fertility were observed in a study in which male and female rats were administered doses of up to 750 mg/kg/day beginning, in males, 9 weeks prior to mating, and in females, 2 weeks prior to mating.

Pregnancy

Teratogenic Effects

Pregnancy Category B.In studies designed to detect effects of isosorbide mononitrate on embryo-fetal development, doses of up to 240 or 248 mg/kg/day, administered to pregnant rats and rabbits, were unassociated with evidence of such effects. These animal doses are about 100 times the maximum recommended human dose (120 mg in a 50 kg woman) when comparison is based on body weight; when comparison is based on body surface area, the rat dose is about 17 times the human dose and the rabbit dose is about 38 times the human dose. There are, however, no adequate and well-controlled studies in pregnant women. Because animal reproduction studies are not always predictive of human response, isosorbide mononitrate extended-release tablets should be used during pregnancy only if clearly needed.

Nonteratogenic Effects

Neonatal survival and development and incidence of stillbirths were adversely affected when pregnant rats were administered oral doses of 750 (but not 300) mg isosorbide mononitrate/kg/day during late gestation and lactation. This dose (about 312 times the human dose when comparison is based on body weight and 54 times the human dose when comparison is based on body surface area) was associated with decreases in maternal weight gain and motor activity and evidence of impaired lactation.

Nursing Mothers

It is not known whether this drug is excreted in human milk. Because many drugs are excreted in human milk, caution should be exercised when ISMN is administered to a nursing mother.

Pediatric Use

The safety and effectiveness of ISMN in pediatric patients have not been established.

Geriatric Use

Clinical studies of isosorbide mononitrate extended-release tablets did not include sufficient information on patients age 65 and over to determine whether they respond differently from younger patients. Other reported clinical experience for isosorbide mononitrate extended-release tablets has not identified differences in response between elderly and younger patients. Clinical experience for organic nitrates reported in the literature identified a potential for severe hypotension and increased sensitivity to nitrates in the elderly. In general, dose selection for an elderly patient should be cautious, usually starting at the low end of the dosing range, reflecting the greater frequency of decreased hepatic, renal, or cardiac function, and of concomitant disease or other drug therapy.

Elderly patients may have reduced baroreceptor function and may develop severe orthostatic hypotension when vasodilators are used. Isosorbide mononitrate extended-release tablets should therefore be used with caution in elderly patients who may be volume depleted, on multiple medications or who, for whatever reason, are already hypotensive. Hypotension induced by isosorbide mononitrate may be accompanied by paradoxical bradycardia and increased angina pectoris.

Elderly patients may be more susceptible to hypotension and may be at a greater risk of falling at therapeutic doses of nitroglycerin.

Nitrate therapy may aggravate the angina caused by hypertrophic cardiomyopathy, particularly in the elderly.

WARNINGS

Amplification of the vasodilatory effects of isosorbide mononitrate by sildenafil can result in severe hypotension. The time course and dose dependence of this interaction have not been studied. Appropriate supportive care has not been studied, but it seems reasonable to treat this as a nitrate overdose, with elevation of the extremities and with central volume expansion.

The benefits of ISMN in patients with acute myocardial infarction or congestive heart failure have not been established; because the effects of isosorbide mononitrate are difficult to terminate rapidly, this drug is not recommended in these settings.

If isosorbide mononitrate is used in these conditions, careful clinical or hemodynamic monitoring must be used to avoid the hazards of hypotension and tachycardia.

General

Severe hypotension, particularly with upright posture, may occur with even small doses of isosorbide mononitrate. This drug should, therefore, be used with caution in patients who may be volume depleted or who, for whatever reason, are already hypotensive. Hypotension induced by isosorbide mononitrate may be accompanied by paradoxical bradycardia and increased angina pectoris.

Nitrate therapy may aggravate the angina caused by hypertrophic cardiomyopathy. In industrial workers who have had long-term exposure to unknown (presumably high) doses of organic nitrates, tolerance clearly occurs. Chest pain, acute myocardial infarction, and even sudden death have occurred during temporary withdrawal of nitrates from these workers, demonstrating the existence of true physical dependence. The importance of these observations to the routine, clinical use of oral isosorbide mononitrate is not known.

ADVERSE REACTIONS

The table below shows the frequencies of the adverse events that occurred in >5% of the subjects in three placebo-controlled North American studies, in which patients in the active treatment arm received 30 mg, 60 mg, 120 mg, or 240 mg of isosorbide mononitrate extended-release tablets once daily. In parentheses, the same table shows the frequencies with which these adverse events were associated with the discontinuation of treatment. Overall, 8% of the patients who received 30 mg, 60 mg, 120 mg, or 240 mg of isosorbide mononitrate in the three placebo-controlled North American studies discontinued treatment because of adverse events. Most of these discontinued because of headache. Dizziness was rarely associated with withdrawal from these studies. Since headache appears to be a dose-related adverse effect and tends to disappear with continued treatment, it is recommended that ISMN treatment be initiated at low doses for several days before being increased to desired levels.

FREQUENCY AND ADVERSE EVENTS (DISCONTINUED)*
Three Controlled North American Studies
Dose | Placebo | 30mg | 60mg | 120mg** | 240mg**
Patients | 96 | 60 | 102 | 65 | 65
Headache | 15%(0%) | 38%(5%) | 51%(8%) | 42%(5%) | 57%(8%)
Dizziness | 4%(0%) | 8%(0%) | 11%(1%) | 9%(2%) | 9%(2%)
*Some individuals discontinued for multiple reasons.
**Patients were started on 60 mg and titrated to their final dose.

In addition, the three North American trials were pooled with 11 controlled trials conducted in Europe. Among the 14 controlled trials, a total of 711 patients were randomized to isosorbide mononitrate extended-release tablets. When the pooled data were reviewed, headache and dizziness were the only adverse events that were reported by >5% of patients. Other adverse events, each reported by ≤5% of exposed patients, and in many cases of uncertain relation to drug treatment, were:

Autonomic Nervous System Disorders:Dry mouth, hot flushes.

Body as a Whole:Asthenia, back pain, chest pain, edema, fatigue, fever, flu-like symptoms, malaise, rigors.

Cardiovascular Disorders, General:Cardiac failure, hypertension, hypotension.

Central and Peripheral Nervous System Disorders:Dizziness, headache, hypoesthesia, migraine, neuritis, paresis, paresthesia, ptosis, tremor, vertigo.

Gastrointestinal System Disorders:Abdominal pain, constipation, diarrhea, dyspepsia, flatulence, gastric ulcer, gastritis, glossitis, hemorrhagic gastric ulcer, hemorrhoids, loose stools, melena, nausea, vomiting.

Hearing and Vestibular Disorders:Earache, tinnitus, tympanic membrane perforation.

Heart Rate and Rhythm Disorders:Arrhythmia, arrhythmia atrial, atrial fibrillation, bradycardia, bundle branch block, extrasystole, palpitation, tachycardia, ventricular tachycardia.

Liver and Biliary System Disorders:SGOT increase, SGPT increase.

Metabolic and Nutritional Disorders:Hyperuricemia, hypokalemia.

Musculoskeletal System Disorders:Arthralgia, frozen shoulder, muscle weakness, musculoskeletal pain, myalgia, myositis, tendon disorder, torticollis.

Myo-, Endo-, Pericardial and Valve Disorders:Angina pectoris aggravated, heart murmur, heart sound abnormal, myocardial infarction, Q wave abnormality.

Platelet, Bleeding and Clotting Disorders:Purpura, thrombocytopenia.

Psychiatric Disorders:Anxiety, concentration impaired, confusion, decreased libido, depression, impotence, insomnia, nervousness, paroniria, somnolence.

Red Blood Cell Disorder:Hypochromic anemia.

Reproductive Disorders, Female:Atrophic vaginitis, breast pain.

Resistance Mechanism Disorders:Bacterial infection, moniliasis, viral infection.

Respiratory System Disorders:Bronchitis, bronchospasm, coughing, dyspnea, increased sputum, nasal congestion, pharyngitis, pneumonia, pulmonary infiltration, rales, rhinitis, sinusitis.

Skin and Appendages Disorders:Acne, hair texture abnormal, increased sweating, pruritus, rash, skin nodule.

Urinary System Disorders:Polyuria, renal calculus, urinary tract infection.

Vascular (Extracardiac) Disorders:Flushing, intermittent claudication, leg ulcer, varicose vein.

Vision Disorders:Conjunctivitis, photophobia, vision abnormal.

In addition, the following spontaneous adverse event has been reported during the marketing of isosorbide mononitrate: syncope.

OVERDOSAGE

Hemodynamic Effects

The ill effects of isosorbide mononitrate overdose are generally the result of isosorbide mononitrate’s capacity to induce vasodilatation, venous pooling, reduced cardiac output, and hypotension. These hemodynamic changes may have protean manifestations, including increased intracranial pressure, with any or all of persistent throbbing headache, confusion, and moderate fever; vertigo, palpitations; visual disturbances; nausea and vomiting (possibly with colic and even bloody diarrhea); syncope (especially in the upright posture); air hunger and dyspnea, later followed by reduced ventilatory effort; diaphoresis, with the skin either flushed or cold and clammy; heart block and bradycardia; paralysis; coma; seizures and death.

Laboratory determinations of serum levels of isosorbide mononitrate and its metabolites are not widely available, and such determinations have, in any event, no established role in the management of isosorbide mononitrate overdose.

There are no data suggesting what dose of isosorbide mononitrate is likely to be life threatening in humans. In rats and mice, there is significant lethality at doses of 2000 mg/kg and 3000 mg/kg, respectively.

No data are available to suggest physiological maneuvers (e.g., maneuvers to change the pH of the urine) that might accelerate elimination of isosorbide mononitrate. In particular, dialysis is known to be ineffective in removing isosorbide mononitrate from the body.

No specific antagonist to the vasodilator effects of isosorbide mononitrate is known, and no intervention has been subject to controlled study as a therapy of isosorbide mononitrate overdose. Because the hypotension associated with isosorbide mononitrate overdose is the result of venodilatation and arterial hypovolemia, prudent therapy in this situation should be directed toward an increase in central fluid volume. Passive elevation of the patient’s legs may be sufficient, but intravenous infusion of normal saline or similar fluid may also be necessary.

The use of epinephrine or other arterial vasoconstrictors in this setting is likely to do more harm than good.

In patients with renal disease or congestive heart failure, therapy resulting in central volume expansion is not without hazard. Treatment of isosorbide mononitrate overdose in these patients may be subtle and difficult, and invasive monitoring may be required.

Methemoglobinemia

Methemoglobinemia has been reported in patients receiving other organic nitrates, and it probably could also occur as a side effect of isosorbide mononitrate. Certainly nitrate ions liberated during metabolism of isosorbide mononitrate can oxidize hemoglobin into methemoglobin. Even in patients totally without cytochrome b5reductase activity, however, and even assuming that the nitrate moiety of isosorbide mononitrate is quantitatively applied to oxidation of hemoglobin, about 2 mg/kg of isosorbide mononitrate should be required before any of these patients manifest clinically significant (≥10%) methemoglobinemia. In patients with normal reductase function, significant production of methemoglobin should require even larger doses of isosorbide mononitrate. In one study in which 36 patients received 2-4 weeks of continuous nitroglycerin therapy at 3.1 to 4.4 mg/hr (equivalent, in total administered dose of nitrate ions, to 7.8 to 11.1 mg of isosorbide mononitrate per hour), the average methemoglobin level measured was 0.2%; this was comparable to that observed in parallel patients who received placebo.

Notwithstanding these observations, there are case reports of significant methemoglobinemia in association with moderate overdoses of organic nitrates. None of the affected patients had been thought to be unusually susceptible.

Methemoglobin levels are available from most clinical laboratories. The diagnosis should be suspected in patients who exhibit signs of impaired oxygen delivery despite adequate cardiac output and adequate arterial pO2. Classically, methemoglobinemic blood is described as chocolate brown without color change on exposure to air. When methemoglobinemia is diagnosed, the treatment of choice is methylene blue, 1 to 2 mg/kg intravenously.

DOSAGE AND ADMINISTRATION

The recommended starting dose of isosorbide mononitrate extended-release tablets is 30 mg (given as a single 30 mg tablet or as 1/2 of a 60 mg tablet) or 60 mg (given as a single tablet) once daily. After several days, the dosage may be increased to 120 mg (given as a single 120 mg tablet or as two 60 mg tablets) once daily. Rarely, 240 mg may be required. The daily dose of isosorbide mononitrate extended-release tablets should be taken in the morning on arising. Isosorbide mononitrate extended-release tablets should not be chewed or crushed and should be swallowed together with a half-glassful of fluid.

HOW SUPPLIED

sosorbide mononitrate extended-release tablets, USP 30 mg are white to off-white, oval shaped, film coated tablets having breakline on one side and debossed ‘3-0’ across breakline and ‘1104’ on other side. They are supplied as follows:

NDC: 70518-2956-00

NDC: 70518-2956-01

PACKAGING: 30 in 1 BLISTER PACK

PACKAGING: 30 in 1 BLISTER PACK

Store at 20°-25°C (68°-77°F), excursions permitted to 15°-30°C (59°-86°F) [see USP Controlled Room Temperature]

Repackaged and Distributed By:

Remedy Repack, Inc.

625 Kolter Dr. Suite #4 Indiana, PA 1-724-465-8762

PACKAGE LABEL

DRUG: ISOSORBIDE MONONITRATE

GENERIC: ISOSORBIDE MONONITRATE

DOSAGE: TABLET, EXTENDED RELEASE

ADMINSTRATION: ORAL

NDC: 70518-2956-0

NDC: 70518-2956-1

COLOR: white

SHAPE: OVAL

SCORE: Two even pieces

SIZE: 9 mm

IMPRINT: 3;0;1104

PACKAGING: 30 in 1 BLISTER PACK

PACKAGING: 30 in 1 BLISTER PACK

ACTIVE INGREDIENT(S):

- ISOSORBIDE MONONITRATE 30mg in 1

INACTIVE INGREDIENT(S):

- CELLULOSE, MICROCRYSTALLINE
- DIETHYL PHTHALATE
- HYDROGENATED CASTOR OIL
- HYDROXYPROPYL CELLULOSE (1600000 WAMW)
- HYPROMELLOSE 2910 (6 MPA.S)
- LACTOSE MONOHYDRATE
- MAGNESIUM STEARATE
- SILICON DIOXIDE
- TALC
- TITANIUM DIOXIDE